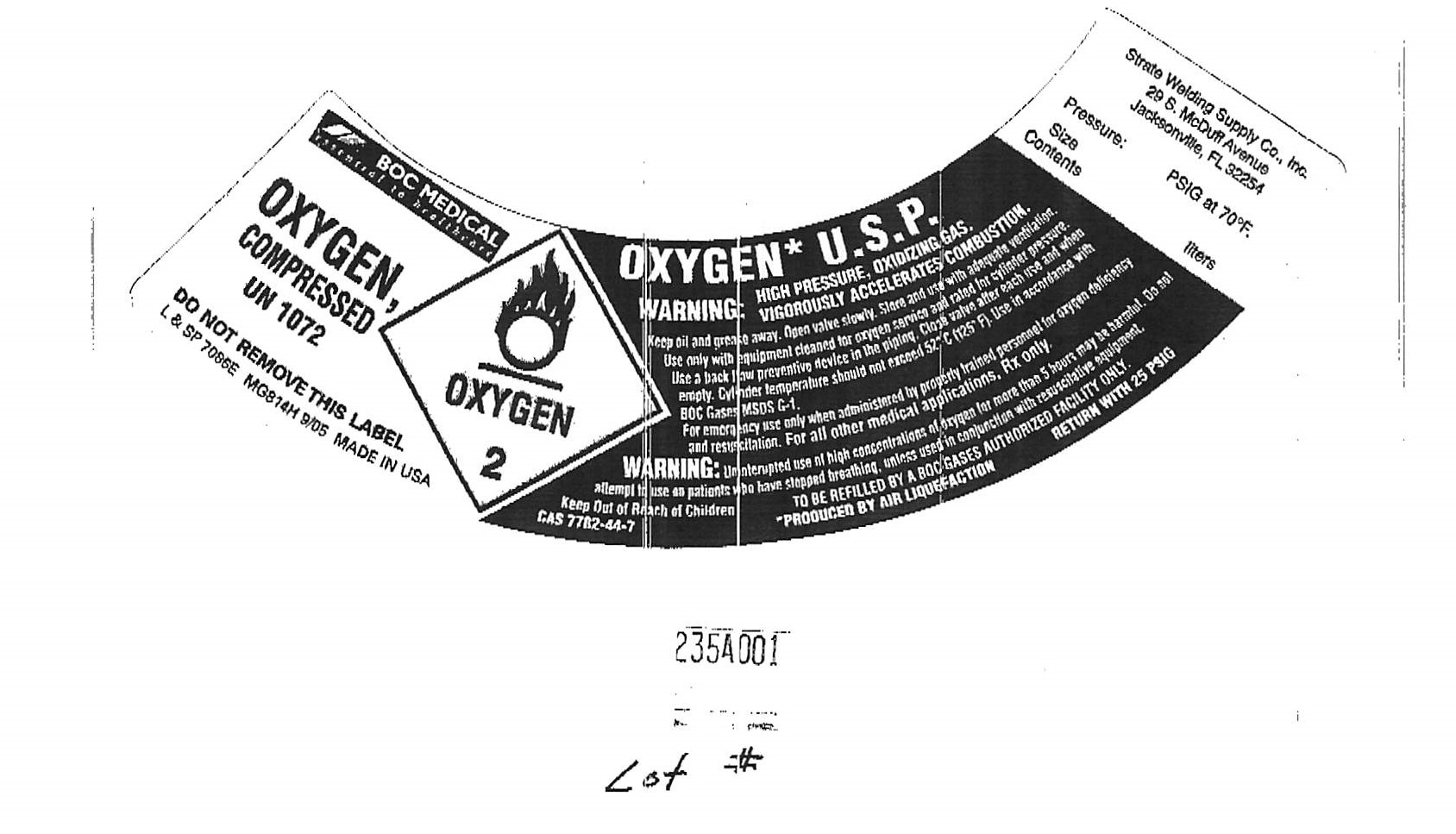 DRUG LABEL: Oxygen
NDC: 48848-001 | Form: GAS
Manufacturer: Strate Welding Supply Co, Inc.
Category: prescription | Type: HUMAN PRESCRIPTION DRUG LABEL
Date: 20251223

ACTIVE INGREDIENTS: OXYGEN 99 L/100 L

Oxygen

Principal for Oxygen Product

OXYGEN
COMPRESSED
UN 1072
DO NOT REMOVE THIS LABEL
L & SP 7086E MG814H 9/05 MADE IN USA
OXYGEN* U.S.P.
WARNING: HIGH PRESSURE, OXIDIZING GAS.
VIGOROUSLY ACCELERATES COMBUSTION.
Keep oil and grease away. Open valve slowly. Store and use with adequate ventilation.
Use only with equipment cleaned for oxygen service and rated for cylinder pressure.
Use a back flow preventative device in the piping. Close valve after each use and when
empty. Cylinder temperature should not exceed 52 C (125 F). Use in accordance with
BOC Gases MSDS G-1.
For emergency use only when administered by properly trained personnel for oxygen deficiency and resuscitation. For all other medical applications, RX only.

WARNING: Uninterrupted use of high concentrations of oxygen for more than 5 hours may be harmful. Do not attempt to use as patients who have stopped breathing, unless used in conjunction with resuscitative equipment.
Keep Out of Reach of Children
TO BE REFILLED BY A BOC AUTHORIZED FACILITY ONLY.
CAS 7782-44-7
*PRODUCED BY AIR LIQUEFICATION
RETURN WITH 25 PSIG